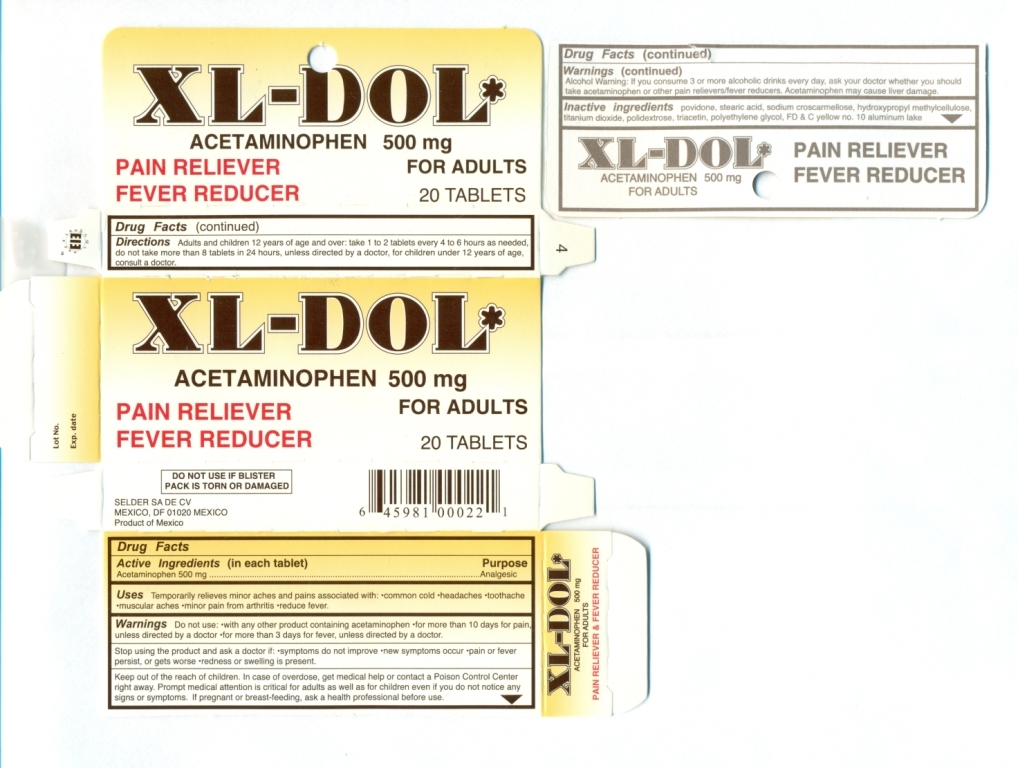 DRUG LABEL: XL-DOL 
NDC: 63654-500 | Form: TABLET
Manufacturer: Selder, S.A. de C.V. 
Category: otc | Type: HUMAN OTC DRUG LABEL
Date: 20111020

ACTIVE INGREDIENTS: ACETAMINOPHEN 500 mg/1 1
INACTIVE INGREDIENTS: POVIDONE; STEARIC ACID; CROSCARMELLOSE SODIUM; HYPROMELLOSES; TITANIUM DIOXIDE; POLYDEXTROSE; TRIACETIN; POLYETHYLENE GLYCOLS; D&C YELLOW NO. 10

Drug Facts

Active Ingredients (in each tablet)
Acetaminophen USP 500 mg

Purpose
Analgesic

INDICATIONS AND USAGE

Uses temporarily relieves minor aches and pains associated with: •common cold •headaches •toothache •muscular aches •minor pain from arthritis •reduce fever

WARNINGS

Warning: Do not use: •with any other product containing acetaminophen •for more than 10 days for pain, unless directed by a doctor •for more than 3 days for fever, unless directed by a doctor

ASK DOCTOR

Stop using the product and ask a doctor if •symptoms do not improve •new symptoms occur •pain or fever persist or gets worse •redness or swelling is present

KEEP OUT OF REACH OF CHILDREN

Keep out the reach of children. In case of overdose, get medical help or contact a Poison Control Center immediately.Prompt medical attention is critical for adults as well as children even if you do not notice any signs or symptoms. If pregnant or breast-feeding, ask a health professional before use.

Alcohol Warning: If you consume 3 or more alcoholic drinks every day, ask your doctor whether you should take acetaminophen or other pain relievers/fever reducers. Acetaminophen may cause liver damage.

INACTIVE INGREDIENT

Inactive Ingredients povidone, stearic acid, sodium croscarmellose, hydroxypropylmethylcellulose, titanium dioxide, polydextrose, triacetin, polyethylene glycol, DC Yellow No.10

DOSAGE AND ADMINISTRATION

Directions Adults and children 12 years and over: take 1 to 2 tablets every 4 to 6 hours as needed, do not take more than 8 tablets in 24 hours unless directed by a doctor, for children under 12 years of age consult a doctor.

Package Label